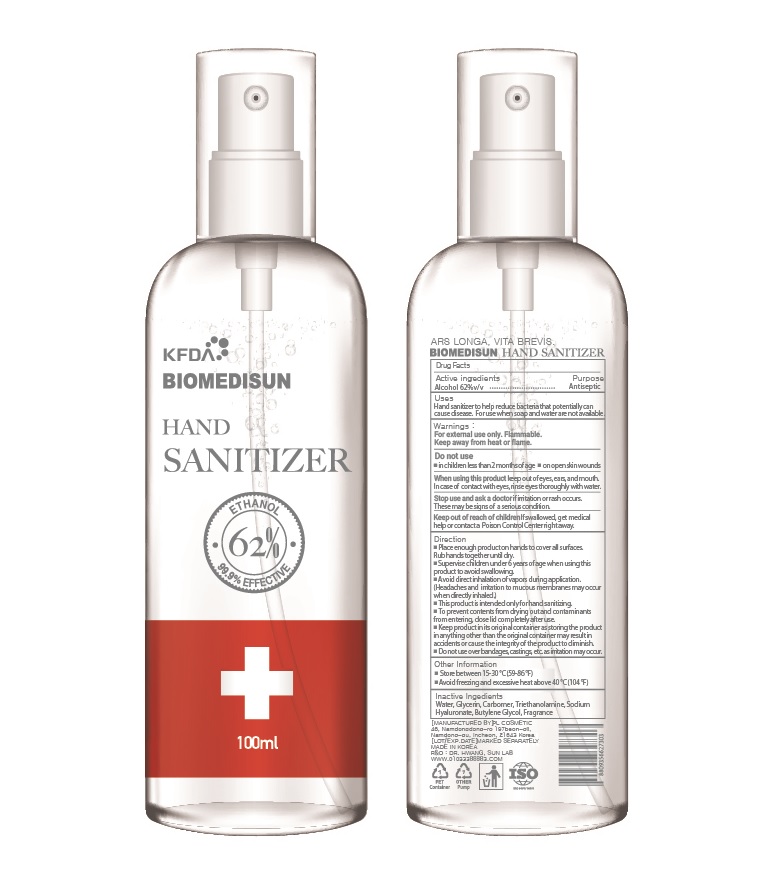 DRUG LABEL: BIOMEDISUN HAND SANITIZER
NDC: 74339-3162 | Form: LIQUID
Manufacturer: PL COSMETIC
Category: otc | Type: HUMAN OTC DRUG LABEL
Date: 20200403

ACTIVE INGREDIENTS: ALCOHOL 62 mL/100 mL
INACTIVE INGREDIENTS: GLYCERIN; CARBOMER HOMOPOLYMER, UNSPECIFIED TYPE; WATER; BUTYLENE GLYCOL; HYALURONATE SODIUM; TROLAMINE

[BIOMEDISUN] 62 % 100 ml MIST TYPE: 74339-3162